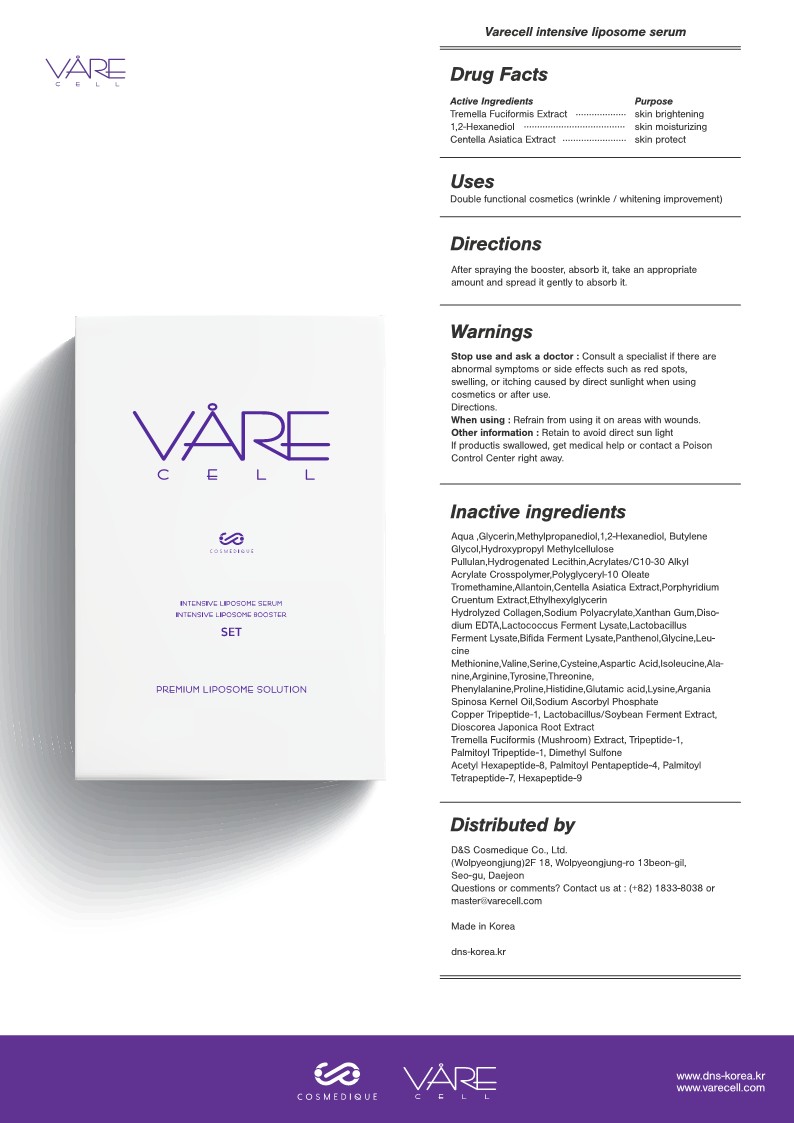 DRUG LABEL: Varecell Intensive Liposome Serum
NDC: 82190-102 | Form: LIQUID
Manufacturer: D&S Cosmedique Co.Ltd
Category: otc | Type: HUMAN OTC DRUG LABEL
Date: 20210819

ACTIVE INGREDIENTS: TREMELLA FUCIFORMIS WHOLE 0.2 g/100 mL; CENTELLA ASIATICA 0.1 g/100 mL; 1,2-HEXANEDIOL 3 g/100 mL
INACTIVE INGREDIENTS: DIOSCOREA JAPONICA ROOT; PALMITOYL TRIPEPTIDE-1; ACETYL HEXAPEPTIDE-8; PALMITOYL TETRAPEPTIDE-7; WATER; BUTYLENE GLYCOL; HYPROMELLOSES; PULLULAN; CARBOMER INTERPOLYMER TYPE A (ALLYL SUCROSE CROSSLINKED); LACTOBACILLUS ACIDOPHILUS; PHENYLALANINE; LYSINE; ARGAN OIL; SODIUM ASCORBYL PHOSPHATE; PREZATIDE COPPER; PALMITOYL PENTAPEPTIDE-4; METHYLPROPANEDIOL; VALINE; SERINE; ASPARTIC ACID; ALANINE; TYROSINE; THREONINE; HISTIDINE; GLUTAMIC ACID; PANTHENOL; LEUCINE; METHIONINE; CYSTEINE; ISOLEUCINE; ARGININE; PROLINE; HYDROGENATED SOYBEAN LECITHIN; POLYGLYCERYL-10 OLEATE; TROMETHAMINE; ALLANTOIN; PORPHYRIDIUM PURPUREUM; ETHYLHEXYLGLYCERIN; COLLAGEN ALPHA-1(I) CHAIN BOVINE; SODIUM POLYACRYLATE (2500000 MW); SODIUM POLYACRYLATE (8000 MW); XANTHAN GUM; EDETATE DISODIUM; LACTOCOCCUS LACTIS; BIFIDOBACTERIUM LONGUM; GLYCERIN; LACTOBACILLUS PLANTARUM; PREZATIDE; DIMETHYL SULFONE; HEXAPEPTIDE-9

82190-102 Varecell Intensive Liposome Serum

Active Ingredients

Tremella Fuciformis Extract 0.2%

1,2-Hexanediol 3%

Centella Asiatica Extract 0.1%

Purpose

Skin Brightening, Anti-wrinkle

Use(s)

Double functional cosmetics (wrinkle / whitening improvement)

Stop Use and Ask a Doctor

If abnormal symptoms or side effects such as red spots, swelling, or itching caused by direct sunlight when using cosmetics or after use.

When using

Refrain from using it on areas with wounds.

Warnings: Other Information

Avoid direct sunlight when using or after use of the product.
If product is swallowed, get medical help or contact a Poison Control Center right away.

Inactive Ingredients

Aqua ,Glycerin,Methylpropanediol,1,2-Hexanediol, Butylene Glycol,Hydroxypropyl Methylcellulose
Pullulan,Hydrogenated Lecithin,Acrylates/C10-30 Alkyl Acrylate Crosspolymer,Polyglyceryl-10 Oleate
Tromethamine,Allantoin,Centella Asiatica Extract,Porphyridium Cruentum Extract,Ethylhexylglycerin
Hydrolyzed Collagen,Sodium Polyacrylate,Xanthan Gum,Diso- dium EDTA,Lactococcus Ferment Lysate,Lactobacillus Ferment Lysate,Bifida Ferment Lysate,Panthenol,Glycine,Leu- cine
Methionine,Valine,Serine,Cysteine,Aspartic Acid,Isoleucine,Ala- nine,Arginine,Tyrosine,Threonine,
Phenylalanine,Proline,Histidine,Glutamic acid,Lysine,Argania Spinosa Kernel Oil,Sodium Ascorbyl Phosphate
Copper Tripeptide-1, Lactobacillus/Soybean Ferment Extract, Dioscorea Japonica Root Extract
Tremella Fuciformis (Mushroom) Extract, Tripeptide-1, Palmitoyl Tripeptide-1, Dimethyl Sulfone
Acetyl Hexapeptide-8, Palmitoyl Pentapeptide-4, Palmitoyl Tetrapeptide-7, Hexapeptide-9

Keep out of reach of children

Directions

After spraying the booster, absorb it, take an appropriate amount and spread it gently to absorb it

other info

Retain to avoid direct sun light If productis swallowed, get medical help or contact a Poison Control Center right away.